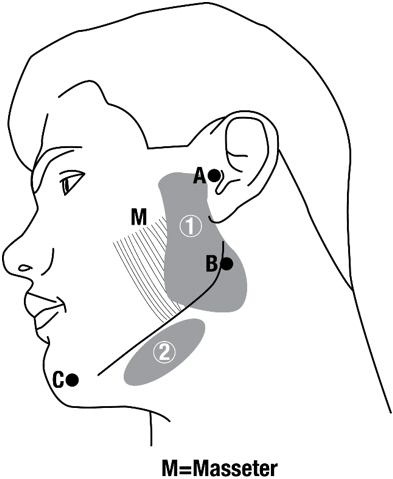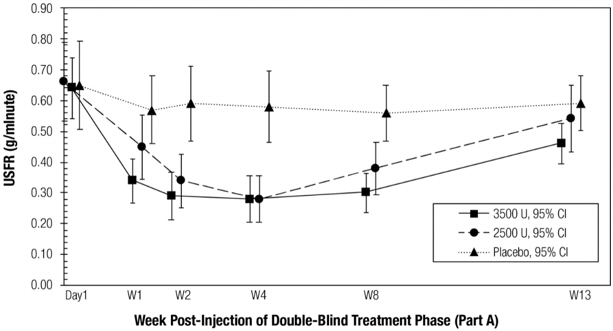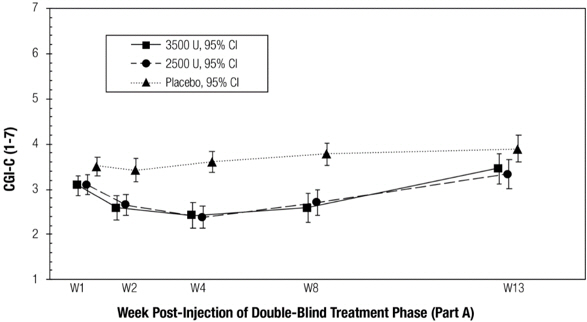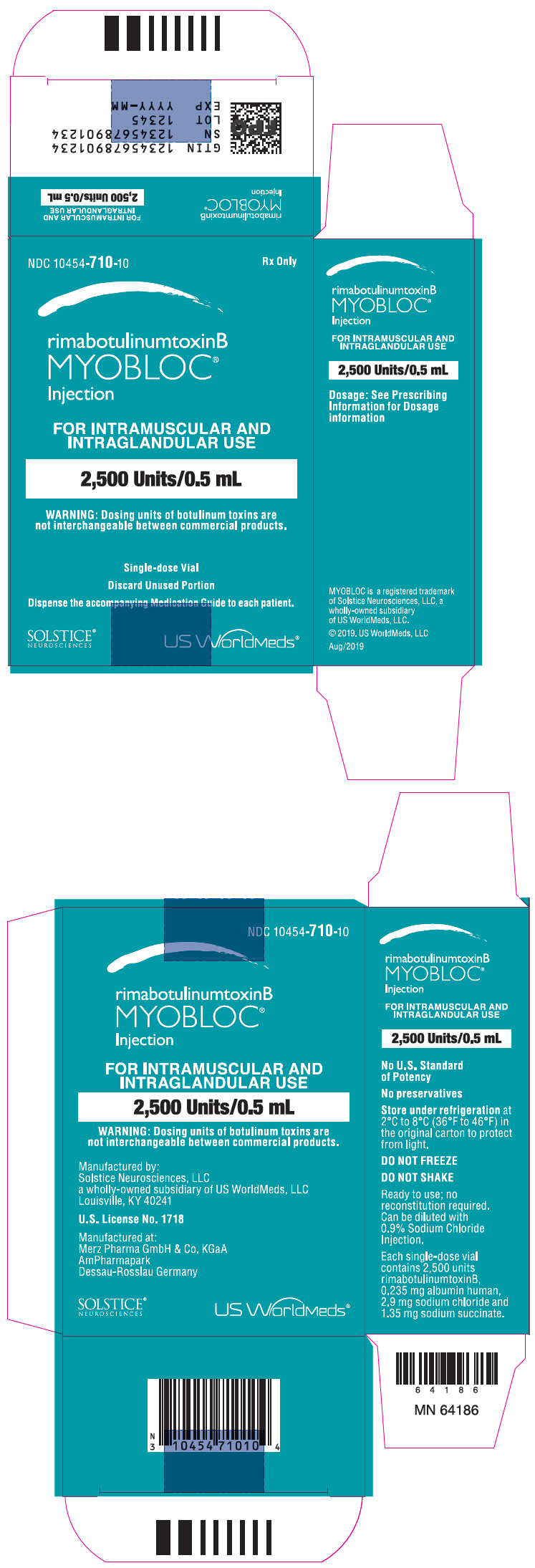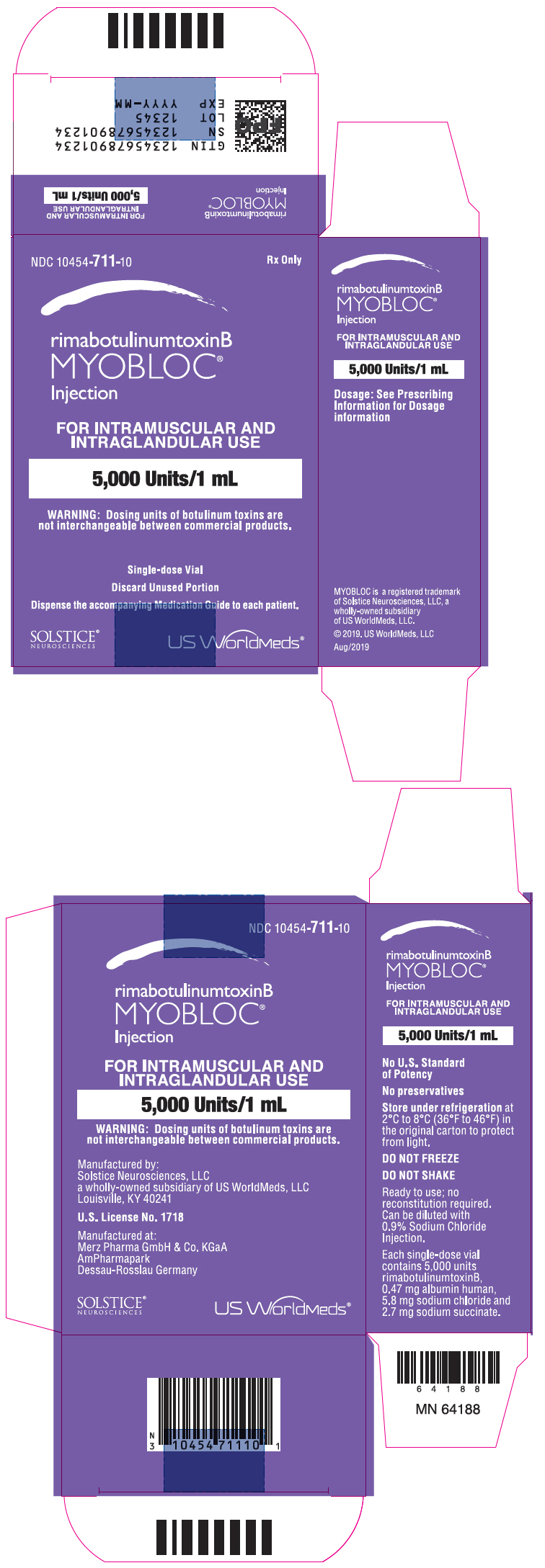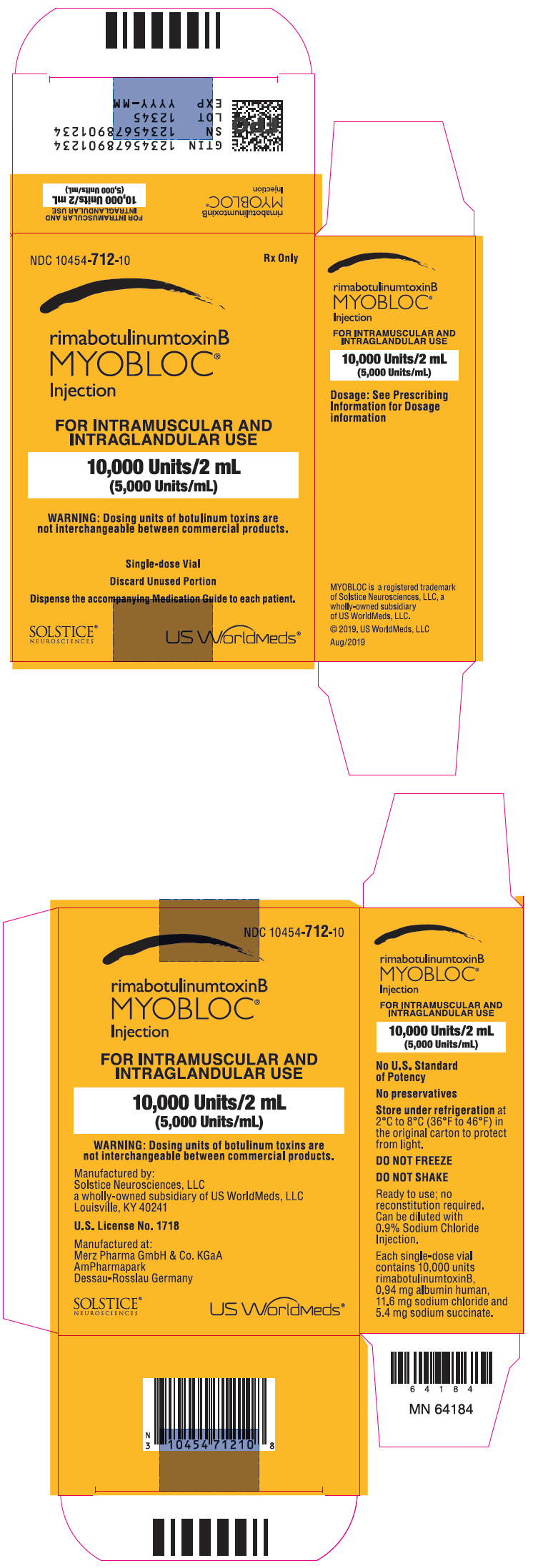 DRUG LABEL: Myobloc
NDC: 10454-710 | Form: INJECTION, SOLUTION
Manufacturer: Solstice Neurosciences, LLC
Category: prescription | Type: HUMAN PRESCRIPTION DRUG LABEL
Date: 20251022

ACTIVE INGREDIENTS: RIMABOTULINUMTOXINB 2500 [USP'U]/0.5 mL
INACTIVE INGREDIENTS: SODIUM SUCCINATE HEXAHYDRATE; SODIUM CHLORIDE; ALBUMIN HUMAN; N-ACETYL-DL-TRYPTOPHAN SODIUM; SODIUM CAPRYLATE; HYDROCHLORIC ACID

HIGHLIGHTS OF PRESCRIBING INFORMATION

These highlights do not include all the information needed to use MYOBLOC® safely and effectively. See full prescribing information for MYOBLOC®.
MYOBLOC® (rimabotulinumtoxinB) injection, for intramuscular or intraglandular use
Initial U.S. Approval: 2000

WARNING: DISTANT SPREAD OF TOXIN EFFECT

See full prescribing information for complete boxed warning.

The effects of MYOBLOC and all botulinum toxin products may spread from the area of injection to produce symptoms consistent with botulinum toxin effects. These symptoms have been reported hours to weeks after injection. Swallowing and breathing difficulties can be life threatening and there have been reports of death. The risk of symptoms is probably greatest in children treated for spasticity but symptoms can also occur in adults, particularly in those patients who have an underlying condition that would predispose them to these symptoms (5.1).

1 INDICATIONS AND USAGE

MYOBLOC is an acetylcholine release inhibitor indicated for:

- Treatment of cervical dystonia to reduce the severity of abnormal head position and neck pain associated with cervical dystonia in adults (1.1)
- Treatment of chronic sialorrhea in adults (1.2)

2 DOSAGE AND ADMINISTRATION

- Cervical Dystonia: for patients with demonstrated tolerance of botulinum toxin injection, recommended total dosage is 2,500 Units to 5,000 Units divided among effected muscles (2.2)
- Chronic Sialorrhea: recommended dosage is 1,500 Units to 3,500 Units; 500 Units to 1,500 Units per parotid gland and 250 Units per submandibular gland; no more frequent than every 12 weeks (2.3)

3 DOSAGE FORMS AND STRENGTHS

Injection: 2,500 Units/0.5 mL; 5,000 Units/mL; or 10,000 Units/2 mL (5,000 Units/mL) in a single-dose vial (3)

4 CONTRAINDICATIONS

MYOBLOC is contraindicated in patients with:

- Known hypersensitivity to any botulinum toxin preparation or to any of the components in the formulation (4, 5.3)
- Infection at the proposed injection site(s) (4)

5 WARNINGS AND PRECAUTIONS

- Spread of toxin effects; swallowing and breathing difficulties can lead to death. Seek immediate medical attention if respiratory, speech or swallowing difficulties occur (5.1, 5.4)
- MYOBLOC potency units cannot be compared to or converted into units of other botulinum toxins (5.2)
- Patients with neuromuscular disorders should be monitored closely for swallowing/breathing difficulty (5.4)

6 ADVERSE REACTIONS

The most common adverse reactions (>5% of MYOBLOC-treated patients at any dose and >5% more common than placebo) include:

- Cervical Dystonia: dry mouth, dysphagia, injection site pain, and headache (6.1)
- Chronic Sialorrhea: dry mouth and dysphagia (6.1)

To report SUSPECTED ADVERSE REACTIONS, contact Solstice Neurosciences at 1-888-461-2255 or FDA at 1-800-FDA-1088 or www.fda.gov/medwatch.

7 DRUG INTERACTIONS

- Co-administration with aminoglycosides or other agents interfering with neuromuscular transmission may potentiate effects of MYOBLOC (7.1)
- Co-administration or overlapping of botulinum toxin serotypes (within 4 months) may potentiate neuromuscular paralysis (7.3)

FULL PRESCRIBING INFORMATION

WARNING: DISTANT SPREAD OF TOXIN EFFECT

Postmarketing reports indicate that the effects of MYOBLOC and all botulinum toxin products may spread from the area of injection to produce symptoms consistent with botulinum toxin effects. These may include asthenia, generalized muscle weakness, diplopia, blurred vision, ptosis, dysphagia, dysphonia, dysarthria, urinary incontinence, and breathing difficulties. These symptoms have been reported hours to weeks after injection. Swallowing and breathing difficulties can be life threatening and there have been reports of death. The risk of symptoms is probably greatest in children treated for spasticity but symptoms can also occur in adults treated for spasticity and other conditions, particularly in those patients who have underlying conditions that would predispose them to these symptoms. In unapproved uses, including spasticity in children and adults, and in approved indications, cases of spread of effect have occurred at doses comparable to those used to treat cervical dystonia and at lower doses [see Warnings and Precautions (5.1)].

1 INDICATIONS AND USAGE

1.1 Cervical Dystonia

MYOBLOC is indicated for the treatment of cervical dystonia to reduce the severity of abnormal head position and neck pain associated with cervical dystonia in adults.

1.2 Chronic Sialorrhea

MYOBLOC is indicated for the treatment of chronic sialorrhea in adults.

2 DOSAGE AND ADMINISTRATION

2.1 Instructions for Safe Use

The potency units of MYOBLOC are specific to the preparation and assay method utilized. They are not interchangeable with other preparations of botulinum toxin products and cannot be compared to or converted into units of any other botulinum toxin products [see Warnings and Precautions (5.2), Description (11)] .

Each single-dose vial should only be used during one session and only for one patient. Discard any remaining solution in the vial.

MYOBLOC is ready to use; no reconstitution required.

MYOBLOC may be diluted with 0.9% Sodium Chloride Injection. Once diluted, the product must be used within 4 hours as the formulation does not contain a preservative.

2.2 Dosing for Cervical Dystonia

The recommended initial dosage of MYOBLOC for cervical dystonia patients with a prior history of tolerating botulinum toxin injections is 2,500 Units to 5,000 Units divided among affected muscles [see Clinical Studies (14.1)] . Patients without a prior history of tolerating botulinum toxin injections should receive a lower initial dosage [see Adverse Reactions (6.1)] . Subsequent dosing should be determined by the patient's individual response. MYOBLOC should be administered by physicians familiar with and experienced in the assessment and management of patients with cervical dystonia.

The duration of effect in patients responding to MYOBLOC treatment for cervical dystonia has been observed in studies to be between 12 and 16 weeks at doses of 5,000 Units or 10,000 Units [see Clinical Studies (14.1)] .

2.3 Dosing for Chronic Sialorrhea

Dosing Information

The recommended dosage of MYOBLOC for chronic sialorrhea is 1,500 Units to 3,500 Units, divided among the parotid and submandibular glands (Table 1). Patient response to treatment should be considered when determining subsequent MYOBLOC dosage [see Clinical Studies (14.2)] . The typical duration of effect of each treatment is up to 3 months; however, the effect may vary in individual patients. The frequency of MYOBLOC repeat treatments should be determined by clinical response but should generally be no more frequent than every 12 weeks.

Table 1: Dosing by Gland for Chronic Sialorrhea in Adults
Gland | Recommended Dosage
Parotid | 500 Units to 1,500 Units per gland
Submandibular | 250 Units per gland

Administration Information

A suitable sterile needle (e.g., 30-gauge, 0.5 inch) should be used for intra-salivary gland administration.

Figure 1: Glands for Injection in Chronic Sialorrhea

Guidelines for locating salivary glands using anatomical landmarks (Figure 1):

- 1. To inject the parotid gland, bisect the distance between the tip of the tragus (Site A) and the angle of the mandible (Site B). Inject one finger breadth anterior to this site (Injection Site 1).
- 2. To inject the submandibular gland, bisect the distance between the angle of the mandible (Site B) and the tip of the chin (Site C). Inject one finger breadth medial to the inferior surface of the point of bisection (Injection Site 2).

In clinical studies, MYOBLOC was injected using anatomical landmarks to localize the salivary glands, or using ultrasound guidance for gland location. Both methods produced similar reduction in the unstimulated salivary flow rate.

3 DOSAGE FORMS AND STRENGTHS

MYOBLOC is a clear and colorless to light-yellow solution available as:

- Injection: 2,500 Units/0.5 mL in a single-dose vial
- Injection: 5,000 Units/mL in a single-dose vial
- Injection: 10,000 Units/2 mL (5,000 Units/mL) in a single-dose vial

4 CONTRAINDICATIONS

MYOBLOC is contraindicated in patients with:

- A known hypersensitivity to any botulinum toxin product or to any of the components in the formulation [see Warnings and Precautions (5.3), Description (11)]
- Infection at the proposed injection site(s)

5 WARNINGS AND PRECAUTIONS

5.1 Spread of Toxin Effect

Postmarketing safety data from MYOBLOC and other approved botulinum toxins suggest that botulinum toxin effects may, in some cases, be observed beyond the site of local injection. The symptoms are consistent with the mechanism of action of botulinum toxin and may include asthenia, generalized muscle weakness, diplopia, blurred vision, ptosis, dysphagia, dysphonia, dysarthria, urinary incontinence, and breathing difficulties. These symptoms have been reported hours to weeks after injection. Swallowing and breathing difficulties can be life threatening and there have been reports of death related to spread of toxin effects. The risk of symptoms is probably greatest in children treated for spasticity, but symptoms can also occur in adults treated for spasticity and other conditions, and particularly in those patients who have underlying conditions that would predispose them to these symptoms. In unapproved uses, including spasticity in children and adults, and in approved indications, symptoms consistent with spread of toxin effect have been reported at doses comparable to or lower than doses used to treat cervical dystonia.

5.2 Lack of Interchangeability between Botulinum Toxin Products

The potency units of MYOBLOC are specific to the preparation and biological activity assay method utilized. Due to differences in the aspects of this assay such as the vehicle, dilution scheme, and laboratory protocols for various potency assays, potency units are not interchangeable with other preparations of botulinum toxin products and, therefore, units of biological activity of MYOBLOC cannot be compared to or converted into units of any other botulinum toxin products assessed with any other specific assay method [see Description (11)] .

5.3 Hypersensitivity Reactions

Serious hypersensitivity reactions have been reported with botulinum toxin products. Angioedema, urticaria, and rash have occurred with MYOBLOC treatment [see Adverse Reactions (6.3)]. Hypersensitivity reactions can also include anaphylaxis, serum sickness, soft tissue edema, and dyspnea. If serious and/or immediate hypersensitivity reactions occur, discontinue further injection of MYOBLOC and institute appropriate medical therapy immediately. The use of MYOBLOC in patients with a known hypersensitivity to any botulinum neurotoxin or to any of the excipients (human albumin, sucrose), could lead to a life-threatening allergic reaction [see Contraindications (4), Adverse Reactions (6.3)].

5.4 Dysphagia and Breathing Difficulties

Treatment with MYOBLOC and other botulinum toxin products can result in swallowing or breathing difficulties. Patients with pre-existing swallowing or breathing difficulties may be more susceptible to these complications. In most cases, this is a consequence of weakening of muscles in the area of injection that are involved in breathing or swallowing. When distant effects occur, additional respiratory muscles may be involved.

Deaths as a complication of severe dysphagia have been reported after treatment with botulinum toxin. Dysphagia may persist for several months and require use of a feeding tube to maintain adequate nutrition and hydration. Aspiration may result from severe dysphagia and is a particular risk when treating patients in whom swallowing or respiratory function is already compromised.

Treatment of cervical dystonia with botulinum toxins may weaken neck muscles that serve as accessory muscles of ventilation. This may result in a critical loss of breathing capacity in patients with respiratory disorders who may have become dependent upon these accessory muscles. There have been postmarketing reports of serious breathing difficulties, including respiratory failure, in cervical dystonia patients. Patients treated with botulinum toxin may require immediate medical attention should they develop problems with swallowing, speech or respiratory disorders. These reactions can occur within hours to weeks after injection with botulinum toxin [see Adverse Reactions (6.1)] .

Individuals with peripheral motor neuropathic diseases, amyotrophic lateral sclerosis, or neuromuscular junctional disorders (e.g., myasthenia gravis or Lambert-Eaton syndrome) should be monitored particularly closely when given botulinum toxin. Patients with neuromuscular disorders may be at increased risk of clinically significant effects including severe dysphagia and respiratory compromise from typical doses of MYOBLOC [see Adverse Reactions (6.1)] .

5.5 Human Albumin and Transmission of Viral Diseases

This product contains albumin, a derivative of human blood. Based on effective donor screening and product manufacturing processes, it carries an extremely remote risk for transmission of viral diseases and variant Creutzfeldt-Jakob disease (vCJD). There is a theoretical risk for transmission of Creutzfeldt-Jakob disease (CJD), but if that risk actually exists, the risk of transmission would be considered extremely remote. No cases of transmission of viral diseases, CJD, or vCJD have ever been identified for licensed albumin or albumin contained in other licensed products.

6 ADVERSE REACTIONS

The following clinically significant adverse reactions to MYOBLOC are discussed in greater detail in other sections of the labeling:

- Spread of Toxin Effect [see Warnings and Precautions (5.1)]
- Lack of Interchangeability Between Botulinum Toxin Products [see Warnings and Precautions (5.2)]
- Hypersensitivity Reactions [see Warnings and Precautions (5.3)]
- Dysphagia and Breathing Difficulties [see Warnings and Precautions (5.4)]
- Human Albumin and Transmission of Viral Diseases [see Warnings and Precautions (5.5)]

6.1 Clinical Trials Experience

Because clinical trials are conducted under widely varying conditions, adverse reaction rates observed in the clinical trials of a drug cannot be directly compared to rates in clinical trials of another drug and may not reflect the rates observed in practice.

Cervical Dystonia

In the treatment of cervical dystonia, MYOBLOC was studied in both placebo-controlled single treatment studies and open-label repeated treatment studies; most treatment sessions and patients were in the uncontrolled studies. The data described below reflect exposure to MYOBLOC at varying dosages in 570 subjects, including more than 300 patients with 4 or more treatment sessions. Most treatment sessions were at dosages of 12,500 Units or less.

Adverse reactions occurring in at least 5% of patients exposed to MYOBLOC treatment in pooled placebo-controlled clinical trials are shown in Table 2. The mean age of the population in these studies was 55 years, and approximately 66% were female. Most of the patients studied were Caucasian, and all had moderate to severe symptoms of cervical dystonia.

The most common adverse reactions (greater than 5% of MYOBLOC-treated patients at any dosage and at least 5% more common than placebo) in studies of cervical dystonia (Studies 1, 2, and 4) were dry mouth, dysphagia, injection site pain, and headache. Dry mouth and dysphagia were the adverse reactions most frequently resulting in discontinuation of treatment. There was an increased incidence of dysphagia with increased dose in the sternocleidomastoid muscle. The incidence of dry mouth showed some dose-related increase with doses injected into the splenius capitis, trapezius, and sternocleidomastoid muscles.

In the cervical dystonia program, only nine patients without a prior history of tolerating injections of type A botulinum toxin have been studied. Adverse reaction rates have not been adequately evaluated in these patients and may be higher than those described in Table 2.

Table 2: Adverse Reactions in at Least 5% of MYOBLOC-Treated Patients and Greater than Placebo, Following Single Treatment Session in Controlled Cervical Dystonia Studies (Studies 1, 2, and 4)
Adverse Reaction | MYOBLOC 2,500 Units (N=31) % | MYOBLOC 5,000 Units (N=67) % | MYOBLOC 10,000 Units (N=106) % | Placebo (N=104) %
Dry Mouth | 3 | 12 | 34 | 3
Dysphagia | 16 | 10 | 25 | 3
Injection Site Pain | 16 | 12 | 15 | 9
Pain | 6 | 6 | 13 | 10
Headache | 10 | 16 | 11 | 8
Dyspepsia | 3 | 0 | 10 | 5
Flu Syndrome | 6 | 9 | 8 | 4
Arthralgia | 0 | 1 | 7 | 5
Back Pain | 3 | 4 | 7 | 3
Cough Increased | 3 | 6 | 7 | 3
Asthenia | 3 | 0 | 6 | 4
Dizziness | 3 | 3 | 6 | 2

In the overall clinical trial experience with MYOBLOC in cervical dystonia (570 patients, including the uncontrolled studies), most cases of dry mouth or dysphagia were reported as mild or moderate in severity. Severe dysphagia was reported by 3% of patients [see Warnings and Precautions (5.4)]. Severe dry mouth was reported by 6% of patients. Dysphagia and dry mouth were the most frequent adverse reactions reported as a reason for discontinuation from repeated treatment studies. These adverse reactions led to discontinuation from further treatments with MYOBLOC in some patients even when not reported as severe.

The following additional adverse events were reported in 2% or greater of patients participating in any of the clinical studies in cervical dystonia (by body system):

Body as a Whole: chest pain, chills, hernia, malaise, abscess, cyst, viral infection; Respiratory: dyspnea, pneumonia; Nervous System: migraine; anxiety, hyperesthesia, vertigo, vasodilation; Digestive System: gastrointestinal disorder; Skin and Appendages: pruritis; Urogenital System: urinary tract infection, cystitis; Special Senses: amblyopia, abnormal vision; Metabolic and Nutritional Disorders: edema; Hemic and Lymphatic System: ecchymosis.

Chronic Sialorrhea

In the double-blind placebo-controlled studies (Study 1 and Study 2), 166 patients were treated with a single treatment of MYOBLOC (1,500 Units; 2,500 Units; or 3,500 Units) and 75 patients received placebo. The mean age of patients treated with MYOBLOC in these studies was 65 years; 83% of the patients were male; and 95% were White. Four MYOBLOC-treated patients and three patients on placebo discontinued because of an adverse event. One patient discontinued because of dry mouth (3,500 Unit dose). The adverse reactions that occurred in at least 5% of MYOBLOC-treated patients and were more frequent than placebo are shown in Table 3.

Table 3: Adverse Reactions in At Least 5% of MYOBLOC-Treated Patients and Greater than Placebo in Pooled Chronic Sialorrhea Studies (Studies 1 and 2)
Adverse Reaction | MYOBLOC 1,500 Units (N=14) [Adverse reactions for 1,500 Unit dose were only evaluated in Study 2] % | MYOBLOC 2,500 Units (N=75) [Adverse reactions for 2,500 Unit and 3,500 Unit doses were evaluated in Studies 1 and 2] % | MYOBLOC 3,500 Units (N=77) % | Placebo (N=75) %
Dry mouth | 14 | 36 | 39 | 7
Dental caries | 0 | 7 | 5 | 3
Dysphagia | 0 | 9 | 4 | 3

6.2 Immunogenicity

As with all therapeutic proteins, there is potential for immunogenicity. The detection of antibody formation is highly dependent on the sensitivity and specificity of the assay. Additionally, the observed incidence of antibody (including neutralizing antibody) positivity in an assay may be influenced by several factors, including assay methodology, sample handling, timing of sample collection, concomitant medications, and underlying disease. For these reasons, comparison of the incidence of antibodies in the studies described below with the incidence of antibodies in other studies or to other rimabotulinumtoxinB products may be misleading.

Cervical Dystonia

A two-stage assay was used to test for immunogenicity and neutralizing activity induced by treatment with MYOBLOC. In order to account for varying lengths of follow-up, life-table analysis methods were used to estimate the rates of development of immune responses and neutralizing activity. During the repeated treatment studies, 446 subjects were followed with periodic ELISA based evaluations for development of antibody responses against MYOBLOC. Only patients who showed a positive ELISA assay were subsequently tested for the presence of neutralizing activity against MYOBLOC in the mouse neutralization assay (MNA). 12% of patients had positive ELISA assays at baseline. Patients began to develop new ELISA responses after a single treatment session with MYOBLOC. By six months after initiating treatment, estimates for ELISA positive rate were 20%, which continued to rise to 36% at one year and 50% positive ELISA status at 18 months. Serum neutralizing activity was primarily not seen in patients until after 6 months. Estimated rates of development were 10% at one year and 18% at 18 months in the overall group of patients, based on analysis of samples from ELISA positive individuals. The effect of conversion to ELISA or MNA positive status on efficacy was not evaluated in these studies, and the clinical significance of development of antibodies has not been determined.

The data reflect the percentage of patients whose test results were considered positive for antibodies to MYOBLOC in both an in vitro and in vivo assay. The results of these antibody tests are highly dependent on the sensitivity and specificity of the assays. Additionally, the observed incidence of antibody positivity in an assay may be influenced by several factors including sample handling, concomitant medications, and underlying disease. For these reasons, comparison of the incidence of antibodies to MYOBLOC with the incidence of antibodies to other products may be misleading.

Chronic Sialorrhea

Immunogenicity potential was not further evaluated for MYOBLOC in the treatment of chronic sialorrhea.

6.3 Postmarketing Experience

The following adverse reactions have been reported during postmarketing use of MYOBLOC: angioedema, urticaria, rash, constipation, dry eye, and accommodation disorder. Because these reactions are reported voluntarily from a population of uncertain size, it is not always possible to reliably estimate their frequency or establish a causal relationship to drug exposure.

7 DRUG INTERACTIONS

7.1 Aminoglycosides and Other Agents Interfering with Neuromuscular Transmission

Co-administration of MYOBLOC and aminoglycosides or other agents interfering with neuromuscular transmission (e.g., curare-like compounds) should only be performed with caution as the effect of the toxin may be potentiated.

7.2 Anticholinergic Drugs

Use of anticholinergic drugs after administration of MYOBLOC may potentiate systemic anticholinergic effects.

7.3 Other Botulinum Neurotoxin Products

The effect of administering different botulinum toxin products at the same time or within several months of each other is unknown. Excessive neuromuscular weakness may be exacerbated by administration of another botulinum toxin prior to the resolution of the effects of a previously administered botulinum toxin.

7.4 Muscle Relaxants

Excessive weakness may also be exaggerated by administration of a muscle relaxant before or after administration of MYOBLOC.

8 USE IN SPECIFIC POPULATIONS

8.1 Pregnancy

Risk Summary

There are no adequate data on the developmental risks associated with the use of MYOBLOC in pregnant women. No developmental toxicity was observed in pregnant rats administered MYOBLOC by intramuscular injection during gestation and lactation, at doses producing maternal toxicity.

In the U.S. general population, the background risk of major birth defects and miscarriage in clinically recognized pregnancies is 2% to 4% and 15% to 20%, respectively. The background risk of major birth defects and miscarriage for the indicated population is unknown.

Data

Animal Data

When MYOBLOC was administered by intramuscular injection to pregnant rats (0, 300, 1000, or 3000 Units/kg/day) or rabbits (0, 0.03, 0.1, 0.3, or 1.0 Units/kg/day) throughout gestation, no adverse effects on embryofetal development were observed. The highest dose tested in rat, which was associated with maternal toxicity, was 36 times the maximum recommended human dose (MRHD) for cervical dystonia (5000 Units) on a body weight (Units/kg) basis. The highest dose tested in rabbit was substantially less than the MRHD for cervical dystonia on a Units/kg basis; maternal toxicity was observed at all but the lowest dose tested.

8.2 Lactation

Risk Summary

There are no data on the presence of MYOBLOC in human milk, the effects on the breastfed infant, or the effects on milk production. The developmental and health benefits of breastfeeding should be considered along with the mother's clinical need for MYOBLOC and any potential adverse effects on the breastfed infant from MYOBLOC or from the underlying maternal condition.

8.4 Pediatric Use

Safety and effectiveness in pediatric patients have not been established.

8.5 Geriatric Use

Cervical Dystonia

In the controlled studies for MYOBLOC in patients with cervical dystonia, 152 (75%) were under the age of 65, and 52 (26%) were 65 years of age or older [see Clinical Studies (14.1)] . For these age groups, the most frequently reported adverse reactions occurred at similar rates in both age groups. Efficacy results did not suggest any large differences between these age groups.

Very few patients age 75 or older were enrolled; therefore, no conclusions regarding the safety and efficacy of MYOBLOC within this age group can be determined.

Chronic Sialorrhea

Of the 166 MYOBLOC-treated patients in the placebo-controlled studies for treatment of chronic sialorrhea [see Clinical Studies (14.2)] , 105 (63%) were 65 years of age or older, and 43 (26%) were 75 years of age or older. No overall differences in safety or effectiveness were observed between patients over 65 years of age and younger patients, but greater sensitivity of some older patients cannot be ruled out.

10 OVERDOSAGE

Excessive doses of MYOBLOC may be expected to produce neuromuscular weakness with a variety of symptoms. Respiratory support may be required where excessive doses cause paralysis of respiratory muscles. In the event of overdose, the patient should be medically monitored for symptoms of excessive muscle weakness or muscle paralysis [see Warnings and Precautions (5.1, 5.4)] . Symptomatic treatment may be necessary.

Symptoms of overdose are likely not to be present immediately following injection. Should accidental injection or oral ingestion occur, the person should be medically supervised for several weeks for signs and symptoms of excessive muscle weakness or muscle paralysis.

In the event of overdose, antitoxin raised against botulinum toxin is available from the Centers for Disease Control and Prevention (CDC) in Atlanta, GA. However, the antitoxin will not reverse any botulinum toxin-induced effects already apparent by the time of antitoxin administration. In the event of suspected or actual cases of botulinum toxin poisoning, please contact your local or state Health Department to process a request for antitoxin through the CDC. If you do not receive a response within 30 minutes, please contact the CDC directly at 770-488-7100. More information can be obtained at http://cdc.gov/ncidod/srp/drugs/drug-service.html.

11 DESCRIPTION

RimabotulinumtoxinB is an acetylcholine release inhibitor. RimabotulinumtoxinB is a 700 kDA botulinum toxin type B complex produced from fermentation of the bacterium Clostridium botulinum type B (Bean strain) and exists in noncovalent association with hemagglutinin and nonhemagglutinin proteins as a neurotoxin complex. The neurotoxin complex is recovered from the fermentation process and purified through a series of precipitation and chromatography steps.

MYOBLOC (rimabotulinumtoxinB) injection is a sterile, preservative-free, clear and colorless to light-yellow solution in a single-dose vial for intramuscular or intraglandular use. Each vial contains 2,500 Units/0.5 mL; 5,000 units/mL; or 10,000 Units/2 mL of rimabotulinumtoxinB at a concentration of 5,000 Units/mL at approximately pH 5.6.

Each 2,500 Units/0.5 mL vial of MYOBLOC contains 2,500 Units rimabotulinumtoxinB, 0.235 mg albumin human, 2.9 mg sodium chloride and 1.35 mg sodium succinate.

Each 5,000 Units/mL vial of MYOBLOC contains 5,000 Units rimabotulinumtoxinB, 0.47 mg albumin human, 5.8 mg sodium chloride and 2.7 mg sodium succinate.

Each 10,000 Units/2 mL vial of MYOBLOC contains 10,000 Units rimabotulinumtoxinB, 0.94 mg albumin human, 11.6 mg sodium chloride and 5.4 mg sodium succinate.

One unit of MYOBLOC corresponds to the calculated median lethal intraperitoneal dose (LD50) in mice. The method for performing the assay is specific to Solstice Neurosciences' manufacture of MYOBLOC. Due to differences in specific details such as the vehicle, dilution scheme and laboratory protocols for various mouse LD50 assays, Units of biological activity of MYOBLOC cannot be compared to or converted into Units of any other botulinum toxin or any toxin assessed with any other specific assay method. Therefore, differences in species sensitivities to different botulinum neurotoxin serotypes preclude extrapolation of animal dose-activity relationships to human dose estimates. The specific activity of MYOBLOC ranges between 70 to 130 Units/ng.

12 CLINICAL PHARMACOLOGY

12.1 Mechanism of Action

MYOBLOC blocks cholinergic transmission at the neuromuscular and salivary neuroglandular junction by inhibiting the release of acetylcholine from peripheral cholinergic nerved terminals. This inhibition occurs according to the following sequence: neurotoxin binding to cholinergic nerve terminals, internalization of the neurotoxin into the nerve terminal, translocation of the light-chain part of the molecule into the cytosol of the nerve terminal, and enzymatic cleavage of synaptic Vesicle Associated Membrane Protein (VAMP, also known as synaptobrevin), a presynaptic target protein essential for the release of acetylcholine. In both muscles and glands, impulse transmission is re-established by the formation of new nerve endings.

12.2 Pharmacodynamics

In responders, the return of increased muscle tone or saliva production typically starts within 3 to 4 months after injection.

12.3 Pharmacokinetics

Using currently available analytical technology, it is not possible to detect MYOBLOC in the peripheral blood following intramuscular or intraglandular injection at the recommended doses.

13 NONCLINICAL TOXICOLOGY

13.1 Carcinogenesis, Mutagenesis, Impairment of Fertility

Carcinogenesis

No long-term carcinogenicity studies in animals have been conducted.

Mutagenesis

No genetic toxicology studies have been conducted.

Impairment of Fertility

Intramuscular administration of MYOBLOC (0, 300, 1000, or 3000 Units/kg/day) to male and female rats prior to and throughout the mating period and continuing in females to gestation day 6 resulted in decreases in implantation sites and viable fetuses at the high dose of 3000 Units/kg/day, which was associated with maternal toxicity. The no-effect dose for reproductive toxicity (1000 Units/kg/day) is 12 times the maximum recommended human dose for cervical dystonia (5000 Units) on a body weight (Units/kg) basis.

14 CLINICAL STUDIES

14.1 Cervical Dystonia

Two Phase 3, randomized, multi-center, double-blind, placebo-controlled studies of the treatment of cervical dystonia were conducted (Study 1 and Study 2). Both studies enrolled only adult patients who had a history of receiving botulinum toxin type A in an open-label manner, with a perceived good response and tolerable adverse effects. Study 1 enrolled patients who were perceived as having an acceptable response to type A toxin, while Study 2 enrolled only patients who had secondarily lost responsiveness to type A toxin. Other eligibility criteria common to both studies were that all patients had moderate or greater severity of cervical dystonia with at least 2 muscles involved, no neck contractures or other causes of decreased neck range of motion, and no history of any other neuromuscular disorder. Patients in Study 1 were randomized to receive placebo, MYOBLOC 5,000 Units or MYOBLOC 10,000 Units. Patients in Study 2 were randomized to receive placebo or 10,000 Units of MYOBLOC. The study agent was administered to subjects in a single treatment session by investigators who selected 2 to 4 muscles per subject from the following: splenius capitis, sternocleidomastoid, levator scapulae, trapezius, semispinalis capitis, and scalene muscles. The total dose was divided between the selected muscles, and from 1 to 5 injections were made per muscle. There were 109 patients enrolled into Study 1, and 77 into Study 2. Patient evaluations continued for 16 weeks post injection.

The primary efficacy outcome variable for both studies was the Toronto Western Spasmodic Torticollis Rating Scale (TWSTRS)-Total Score (scale range of possible scores is 0–87) at Week 4. TWSTRS is comprised of three sub-scales which examine 1) Severity—the severity of the patient's abnormal head position; 2) Pain—the severity and duration of pain due to the dystonia; and 3) Disability— the effects of the abnormal head position and pain on a patient's activities. The secondary endpoints were the Patient Global and Physician Global Assessments of change at Week 4. Both Global Assessments used a 100-point visual-analog scale (VAS). The Patient Global Assessment allows patients to indicate how they feel at the time of their evaluation compared to the pre-injection baseline. Likewise, the Physician Global Assessment indicates the physician's assessment of a patient's change from baseline to Week 4. Scores of 50 indicate no change, 0 much worse, and 100 much better. Results of comparisons of the primary and secondary efficacy variables are summarized in Table 4.

Table 4: Efficacy Results From Two Phase 3 MYOBLOC Studies in Cervical Dystonia
 | STUDY 1 |  |  | STUDY 2
Assessments [95% Cl are for the differences between the active and placebo groups. The P values are for the comparison of active dose and placebo. For TWSTRS-Total and TWSTRS-subscale scores, P values are from ANCOVA for each variable with center and treatment in the model and the baseline value of the variable included as a covariate. For the Patient Global and Physician Global Assessments, P values are from ANOVA for each variable with center and treatment in the model.] | Placebo (N=36) | MYOBLOC 5,000 Units (N=36) | MYOBLOC 10,000 Units (N=37) | Placebo (N=38) | MYOBLOC 10,000 Units (N=39)
TWSTRS Total
Mean at Baseline | 43.6 | 46.4 | 46.9 | 51.2 | 52.8
Change from Baseline | -4.3 | -9.3 | -11.7 | -2.0 | -11.1
95% Confidence Interval |  | (-8.9, -1.2) | (-11.1, -3.3) |  | (-12.2, -5.2)
P value |  | 0.012 | 0.0004 |  | 0.0001
Patient Global
Mean at Week Four | 43.6 | 60.6 | 64.6 | 39.5 | 60.2
95% Confidence Interval |  | (7.0, 26.9) | (11.3, 31.1) |  | (11.2, 29.1)
P value |  | 0.001 | 0.0001 |  | 0.0001
Physician Global
Mean at Week Four | 52.0 | 65.3 | 64.2 | 47.9 | 60.6
95% Confidence Interval |  | (5.5, 21.3) | (3.9, 19.7) |  | (7.4, 18.1)
P value |  | 0.001 | 0.004 |  | 0.0001
TWSTRS-Subscales
– Severity
Mean at Baseline | 18.4 | 20.2 | 20.2 | 22.1 | 22.6
Change from Baseline | -2.3 | -3.2 | -4.8 | -1.2 | -3.7
95% Confidence Interval |  | (-2.5, 0.6) | (-4.0, -1.0) |  | (-3.9, -1.0)
P value |  | 0.22 | 0.002 |  | 0.001
– Pain
Mean at Baseline | 10.9 | 11.8 | 12.4 | 12.2 | 11.9
Change from Baseline | -0.5 | -3.6 | -4.2 | -0.2 | -3.6
95% Confidence Interval |  | (-4.7, -1.1) | (-5.1, -1.4) |  | (-5.0, -2.1)
P value |  | 0.002 | 0.0008 |  | 0.0001
– Disability
Mean at Baseline | 14.3 | 14.4 | 14.4 | 16.9 | 18.3
Change from Baseline | -1.6 | -2.5 | -2.7 | 0.8 | -3.8
95% Confidence Interval |  | (-2.7, 0.7) | (-2.8, 0.6) |  | (-4.1, -1.0)
P value |  | 0.26 | 0.19 |  | 0.002

There were no statistically significant differences in results between the 5,000 Unit and 10,000 Unit doses in Study 1. Exploratory analyses of these two studies suggested that the majority of patients who showed a beneficial response by Week 4 had returned to their baseline status between Weeks 12 to 16 post injection. Although there was a MYOBLOC-associated decrease in pain, there remained many patients who experienced an increase in dystonia-related neck pain irrespective of treatment group [ See Adverse Reactions, (6.1)] . TWSTRS Total Score at Week 4 and Patient Global Assessment among subgroups by gender or age showed consistent treatment-associated effects across these subgroups [see Use in Specific Populations (8.5)]. There were too few non-Caucasian patients enrolled to draw any conclusions regarding relative efficacy in racial subsets.

MYOBLOC was studied in two Phase 2 dose-ranging studies, Studies 3 and 4, which preceded the Phase 3 studies. Studies 3 and 4 had a study design similar to the Phase 3 studies, including eligibility criteria. Study 3 enrolled 85 patients randomized to placebo, MYOBLOC 400 Units, MYOBLOC 1,200 Units, or MYOBLOC 2,400 Units (21 or 22 patients per group). Study 4 enrolled 122 patients randomized to placebo, MYOBLOC 2,500 Units, MYOBLOC 5,000 Units, or MYOBLOC 10,000 Units (30 or 31 patients per group). These studies demonstrated efficacy on the TWSTRS-Total, baseline to Week 4, at doses of 2,400 Units; 2,500 Units; 5,000 Units; and 10,000 Units. Study 3 showed mean improvement from baseline on the Week 4 TWSTRS for placebo and 2,400 Units of 2.0 and 8.5 points respectively (from baselines of 42.0 and 42.4 points). Study 4 showed mean improvement from baseline to Week 4 for placebo, MYOBLOC 2,500 Units, MYOBLOC 5,000 Units, and MYOBLOC 10,000 Units of 3.3, 11.6, 12.5, and 16.4 points, respectively (from baseline of 45.5, 45.6, 45.2, and 47.5 points). Study 3 also showed less response for doses below 2,400 Units.

Study 5 was an open-label, intrapatient dose-escalation study of 3 treatment sessions where each patient with cervical dystonia sequentially received 10,000 Units; 12,500 Units; and 15,000 Units of MYOBLOC, at periods of 12 to 16 weeks between treatment sessions irrespective of their response to their previous dose. This study enrolled 145 patients, of whom 125 received all three treatments. Although this was an open-label design where investigators and patients knew the dose at each treatment session, there were similar mean improvements on the TWSTRS-Total, from baseline to Week 4, for all three doses.

In the MYOBLOC-treated patients (n=112) of the Phase 3 studies, 19% had 2 muscles injected, 48% had 3 muscles injected, and 33% had 4 muscles injected. Table 5 indicates the frequency of use for each of the permitted muscles, and the fraction of the total dose of the treatment injected into each muscle, for those patients in whom the muscle was injected.

Table 5: Study 1 and Study 2 Combined Data Fraction of Total Dose Injected into Involved Muscles in Patients with Cervical Dystonia
Muscle Injected | Percent Frequency Injected [Percent frequency of patients in whom each muscle was injected] | Fraction of Total Dose Injected by Percentiles
Muscle Injected | Percent Frequency Injected [Percent frequency of patients in whom each muscle was injected] | 25th | 50th | 75th
Splenius Capitis | 88 | 0.30 | 0.40 | 0.50
Sternocleidomastoid | 80 | 0.20 | 0.25 | 0.30
Semispinalis Capitis | 52 | 0.30 | 0.36 | 0.50
Levator Scapulae | 46 | 0.13 | 0.20 | 0.20
Trapezius | 38 | 0.20 | 0.25 | 0.35
Scalene Complex | 13 | 0.20 | 0.25 | 0.30

14.2 Chronic Sialorrhea

Study 1

Study 1 (NCT01994109) was a multicenter, randomized, double-blind, placebo-controlled study of a single treatment of chronic sialorrhea (with 13-week follow-up), followed by an open-label treatment period. 187 adult patients with chronic, troublesome sialorrhea for at least 3 months were randomized to receive treatment with MYOBLOC 2,500 Units, MYOBLOC 3,500 Units, or placebo. Patients had chronic sialorrhea associated with Parkinson's disease (n=122), amyotrophic lateral sclerosis(ALS) (n=12), stroke (n=13), and other causes (n=40). Patients with a history of aspiration or severe dysphagia in the last 6 months and ALS patients with a forced vital capacity of less than 20% of predicted were excluded from the study. A single treatment was administered, consisting of bilateral injections of MYOBLOC into the parotid (1,000 Units or 1,500 Units per gland) and submandibular (250 Units per gland) salivary glands or volume matched placebo. A total of 114 patients received 4 consecutive treatments with 3,500 Units of MYOBLOC every 11 to 15 weeks.

The co-primary efficacy endpoints for Study 1 were the change from baseline in Unstimulated Salivary Flow Rate (USFR) and the Clinical Global Impression of Change (CGI-C) assessed 4 weeks after treatment in the double-blind part of the study. The CGI-C is a seven-point Likert scale with scores ranging from "1=very much improved" to "7=very much worse". The change from baseline (i.e., decrease) in USFR at Week 4 was significantly greater for patients treated with MYOBLOC than in patients on placebo (Table 6). Similarly, CGI-C scores at Week 4 were significantly lower (i.e., better) in patients treated with MYOBLOC than in patients on placebo (Table 7). Chronic sialorrhea was 'much improved' or 'very much improved', according to CGI-C scores at Week 4 post injection, in patients treated with MYOBLOC 2,500 Units (60%) and MYOBLOC 3,500 Units (53%) than in patients on placebo (12%).

Figure 2 and Figure 3 show change in the USFR and CGI-C, respectively over the 13-week double-blind part of Study 1. The change from baseline to Week 4 on the USFR and the CGI-C was similar for MYOBLOC 2,500 Units and 3,500 Units, but there was a trend for more prolonged effect in patients treated with MYOBLOC 3,500 Units (Figure 2). CGI-C scores over the double-blind period were similar for both dose groups (Figure 3).

Table 6: Mean USFR Change from Baseline (g/min) at Week 4 in Study 1
Visit | MYOBLOC 2,500 Units (N=63) | MYOBLOC 3,500 Units (N=64) | Placebo (N=57)
Week 4 | -0.37 [Primary endpoint, p< 0.0001] | -0.36 | -0.07

Table 7: CGI-C Score at Week 4 in Study 1
Visit | MYOBLOC 2,500 Units (N=63) | MYOBLOC 3,500 Units (N=64) | Placebo (N=57)
Week 4 | 2.38 [Co-primary endpoint, p< 0.0001] | 2.45 | 3.59

Figure 2: Mean Unstimulated Salivary Flow Rate over Time in Study 1

Figure 3: Mean Clinical Global Impression of Change Score over Time in Study 1

Study 2

Study 2 (NCT00515437) was a multicenter, double-blind, placebo-controlled, sequential dose-escalation study of MYOBLOC 1,500 Units; 2,500 units; or 3,500 Units versus matching placebo for the treatment of troublesome chronic sialorrhea in patients with Parkinson's disease. Patients were randomized to receive a single treatment with MYOBLOC 1,500 Units (n=14); MYOBLOC 2,500 Units (n=12); or MYOBLOC 3,500 Units (n=13). Each group also included 5 patients who received placebo (n=15). Patients were followed for up to 20 weeks after injection. The mean age of patients in the study was 71 years. In the study, 89% of patients were male, and 96% White.

The change from baseline in the unstimulated salivary flow rate (USFR) and the Clinical Global Impression of Change (CGI-C) was assessed 4 weeks after treatment. There was a significant reduction in the USFR for all three dosage groups of MYOBLOC, compared with patients on placebo (Table 8). Similarly, the CGI-C scores were significantly lower in all three MYOBLOC dosage groups than in patients on placebo (Table 9). The mean change from baseline to Week 4 on the USFR was similar in all three MYOBLOC dosage groups.

Table 8: Mean USFR Change from Baseline (g/min) at Week 4 in Study 2
Visit | MYOBLOC 1,500 Units (N=14) | MYOBLOC 2,500 Units (N=12) | MYOBLOC 3,500 Units (N=13) | Placebo (N=14)
Week 4 | -0.44 [Nominal p-value <0.0001;] | -0.38 | -0.30 [Nominal p-value < 0.001] | 0.01

Table 9: CGI-C Score at Week 4 in Study 2
Visit | MYOBLOC 1,500 Units (N=14) | MYOBLOC 2,500 Units (N=12) | MYOBLOC 3,500 Units (N=13) | Placebo (N= 14)
Week 4 | 2.14 [Nominal p-value < 0.0001] | 2.00 | 1.62 | 3.93

16 HOW SUPPLIED/STORAGE AND HANDLING

16.1 How Supplied

MYOBLOC (rimabotulinumtoxinB) injection is supplied as a clear and colorless to light-yellow solution in single-dose glass vials.

MYOBLOC is available in three presentations (Table 10).

Table 10: MYOBLOC Presentations
Strength per Vial | Single-Vial Carton
2,500 Units/0.5 mL | NDC 10454-710-10
5,000 Units/mL | NDC 10454-711-10
10,000 Units/2 mL | NDC 10454-712-10

No U.S. Standard of Potency

16.2 Storage and Handling

Store under refrigeration at 2°C to 8°C (36°F- 46°F) in the original carton to protect from light.

DO NOT FREEZE. DO NOT SHAKE.

All vials of expired MYOBLOC and equipment used in the administration of MYOBLOC should be carefully discarded according to standard medical waste practices.

Do not use after the expiration date stamped on the vial.

17 PATIENT COUNSELING INFORMATION

Advise the patient to read the FDA-approved patient labeling (Medication Guide).

Swallowing, Speaking, or Breathing Difficulties or Other Unusual Symptoms

Advise patients to inform their healthcare provider if they develop any unusual symptoms, including difficulty with swallowing, speaking or breathing, or if any existing symptom worsens [see Box Warning and Warnings and Precautions (5.1, 5.4)]. Inform patients of the risk of aspiration.

Ability to Operate Machinery or Vehicles

Counsel patients that if loss of strength, muscle weakness, or impaired vision occur, they should avoid driving a car or engaging in other potentially hazardous activities.

Manufactured By:

Solstice Neurosciences, LLC, Rockville, MD 20852

U.S. License No. 1718

"MYOBLOC" and the "MYOBLOC Logo" are registered trademarks of Solstice Neurosciences, Inc.

Protected by U.S. Patent No.
6,290,961; 6,632,433; 6,872,397; 6,887,476

© 2019 Solstice Neurosciences, LLC

64183

RA-MYO-V5

MEDICATION GUIDE
MYOBLOC® (My-o-block)
(rimabotulinumtoxinB)
injection, for intramuscular or intraglandular use

What is the most important information I should know about MYOBLOC?

MYOBLOC may cause serious side effects that can be life threatening. Call your doctor or get medical help right away if you have any of these problems after treatment with MYOBLOC:

- Problems swallowing, speaking, or breathing. These problems can happen hours to weeks after an injection of MYOBLOC if the muscles that you use to breathe and swallow become weak after the injection. Death can happen as a complication if you have severe problems with swallowing or breathing after treatment with MYOBLOC.
  - People with certain breathing problems may need to use muscles in their neck to help them breathe. These people may be at greater risk for serious breathing problems with MYOBLOC.
  - Swallowing problems may last for several months. People who cannot swallow well may need a feeding tube to receive food and water. If swallowing problems are severe, food or liquids may go into your lungs. People who already have swallowing or breathing problems before receiving MYOBLOC have the highest risk of getting these problems.
- Spread of toxin effects. In some cases, the effect of botulinum toxin may affect areas of the body away from the injection site and cause symptoms of a serious condition called botulism. The symptoms of botulism include:

- loss of strength and muscle weakness all over the body
- double vision
- blurred vision and drooping eyelids
- hoarseness or change or loss of voice (dysphonia)

- trouble saying words clearly (dysarthria)
- loss of bladder control
- trouble breathing
- trouble swallowing (dysphagia)

These symptoms can happen hours to weeks after you receive an injection of MYOBLOC.

These problems could make it unsafe for you to drive a car or do other dangerous activities. See " What should I avoid while receiving MYOBLOC?"

What is MYOBLOC?

MYOBLOC is a prescription medicine used in adults that is injected into:

- muscles and used to treat the abnormal head position and neck pain that happens with cervical dystonia (CD).
- glands that make saliva and is used to treat long-lasting (chronic) drooling (sialorrhea).

It is not known whether MYOBLOC is safe or effective in children.

Do not receive MYOBLOC if you:

- are allergic to MYOBLOC or any of the ingredients in MYOBLOC. See the end of this Medication Guide for a list of ingredients in MYOBLOC.
- had an allergic reaction to any other botulinum toxin product such as BOTOX® , BOTOX® Cosmetic (onabotulinumtoxinA), DYSPORT® (abobotulinumtoxinA), or XEOMIN® (incobotulinumtoxinA).
- have a skin infection at the planned injection site.

Before receiving MYOBLOC, tell your doctor about all your medical conditions, including if you have:

- a disease that affects your muscles and nerves (such as amyotrophic lateral sclerosis [ALS or Lou Gehrig's disease], myasthenia gravis or Lambert-Eaton syndrome). See " What is the most important information I should know about MYOBLOC?"
- had any side effect from any botulinum toxin product in the past.
- a breathing problem, such as asthma or emphysema.
- a history of swallowing problems or inhaling food or fluid into your lungs (aspiration).
- bleeding problems.
- drooping eyelids.
- plans to have surgery.
- had surgery on your face.

Tell your doctor if you:

- are pregnant or plan to become pregnant. It is not known if MYOBLOC can harm your unborn baby.
- are breastfeeding or plan to breastfeed. It is not known if MYOBLOC passes into breast milk.

Tell your doctor about all the medicines you take, including prescription and over-the-counter medicines, vitamins and herbal supplements. Talk to your doctor before you take any new medicine after you receive MYOBLOC.

Using MYOBLOC with certain other medicines may cause serious side effects. Do not start any new medicines until you have told your doctor that you have received MYOBLOC in the past. Especially tell your doctor if you:

- have received any other botulinum toxin product in the last 4 months.
- have received injections of botulinum toxin such as BOTOX®, BOTOX® Cosmetic (onabotulinumtoxinA), DYSPORT® (abobotulinumtoxinA), or XEOMIN® (incobotulinumtoxinA) in the past. Be sure your doctor knows exactly which product you received.
- have recently received an antibiotic by injection.
- take muscle relaxants.
- take an allergy or cold medicine.
- take a sleep medicine.

Ask your doctor if you are not sure if your medicine is one that is listed above.

Know the medicines you take. Keep a list of your medicines with you to show your doctor and pharmacist each time you get a new medicine.

How should I receive MYOBLOC?

- MYOBLOC is a shot (injection) that your doctor will give you.
- MYOBLOC is injected into your affected muscles or glands.
- Your doctor may give you another dose of MYOBLOC after 12 weeks or longer, if it is needed.
- Your doctor may change your dose of MYOBLOC, until you and your doctor find the best dose for you.

What should I avoid while receiving MYOBLOC?

MYOBLOC may cause loss of strength or general muscle weakness or vision problems within hours to weeks of receiving MYOBLOC. If this happens, do not drive a car, operate machinery or do other dangerous activities. See " What is the most important information I should know about MYOBLOC?"

What are the possible side effects of MYOBLOC?

MYOBLOC can cause serious side effects including:

See " What is the most important information I should know about MYOBLOC?"

- allergic reactions. Symptoms of an allergic reaction to MYOBLOC may include: itching, rash, redness, swelling, wheezing, trouble breathing, or dizziness or feeling faint. Tell your doctor or get medical help right away if you get wheezing, or trouble breathing, or if you get dizzy or faint.

The most common side effects of MYOBLOC in people with cervical dystonia include:

- dry mouth

- injection site discomfort or pain

- trouble swallowing (dysphagia)

- headache

The most common side effects of MYOBLOC in people with sialorrhea include dry mouth and trouble swallowing (dysphagia).

These are not all the possible side effects of MYOBLOC. Call your doctor for medical advice about side effects. You may report side effects to FDA at 1-800-FDA-1088. You may also report side effects to Solstice Neurosciences at 1-888-461-2255.

General information about the safe and effective use of MYOBLOC.

Medicines are sometimes prescribed for purposes other than those listed in a Medication Guide.

You can ask your doctor or pharmacist for information about MYOBLOC that is written for healthcare professionals.

What are the ingredients in MYOBLOC?

Active ingredient: botulinum toxin type B

Inactive ingredients: albumin human, sodium chloride and sodium succinate.

Manufactured by: Solstice Neurosciences, LLC, Rockville MD 20852
U.S. License No. 1718
SNI-MYO424A-0410
RA-MYO-MGV2
"MYOBLOC" and the "MYOBLOC Logo" are registered trademarks of Solstice Neurosciences, LLC
All trademarks are the property of their respective owners.

For more information about MYOBLOC call 1-888-461-2255 or go to www.MYOBLOC.com.

This Medication Guide has been approved by the U.S. Food and Drug Administration.

Rev: 3/2021

PRINCIPAL DISPLAY PANEL - 0.5 mL Vial Carton

NDC 10454-710-10

Rx Only

rimabotulinumtoxinB
MYOBLOC®
Injection

FOR INTRAMUSCULAR AND
INTRAGLANDULAR USE

2,500 Units/0.5 mL

WARNING: Dosing units of botulinum toxins are
not interchangeable between commercial products.

Single-dose Vial

Discard Unused Portion

Dispense the accompanying Medication Guide to each patient.

SOLSTICE®
NEUROSCIENCES

US WorldMeds®

PRINCIPAL DISPLAY PANEL - 1 mL Vial Carton

NDC 10454-711-10

Rx Only

rimabotulinumtoxinB
MYOBLOC®
Injection

FOR INTRAMUSCULAR AND
INTRAGLANDULAR USE

5,000 Units/1 mL

WARNING: Dosing units of botulinum toxins are
not interchangeable between commercial products.

Single-dose Vial

Discard Unused Portion

Dispense the accompanying Medication Guide to each patient.

SOLSTICE®
NEUROSCIENCES

US WorldMeds®

PRINCIPAL DISPLAY PANEL - 2 mL Vial Carton

NDC 10454-712-10

Rx Only

rimabotulinumtoxinB
MYOBLOC®
Injection

FOR INTRAMUSCULAR AND
INTRAGLANDULAR USE

10,000 Units/2 mL
(5,000 Units/mL)

WARNING: Dosing units of botulinum toxins are
not interchangeable between commercial products.

Single-dose Vial

Discard Unused Portion

Dispense the accompanying Medication Guide to each patient.

SOLSTICE®
NEUROSCIENCES

US WorldMeds®